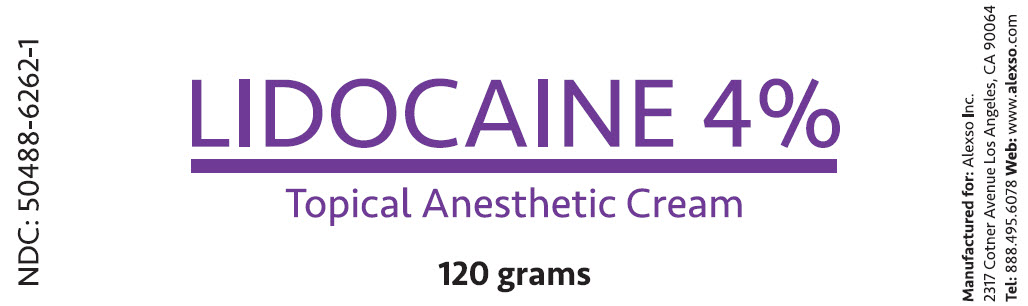 DRUG LABEL: Lidocaine 4%
NDC: 50488-6262 | Form: CREAM
Manufacturer: Alexso Inc.
Category: otc | Type: HUMAN OTC DRUG LABEL
Date: 20190212

ACTIVE INGREDIENTS: LIDOCAINE 4 g/100 g
INACTIVE INGREDIENTS: WATER; ARNICA MONTANA FLOWER; INDIAN FRANKINCENSE; CETOSTEARYL ALCOHOL; CHONDROITIN SULFATE (BOVINE); DIMETHYL SULFONE; ETHYLHEXYLGLYCERIN; GLUCOSAMINE SULFATE; GLYCERIN; GLYCERYL 1-STEARATE; C13-14 ISOPARAFFIN; ISOSTEARYL PALMITATE; LAURETH-7; PEG-100 STEARATE; PHENOXYETHANOL; POLYACRYLAMIDE (10000 MW); PROPYLENE GLYCOL; SODIUM POLYACRYLATE (2500000 MW); STEARIC ACID; TROLAMINE

Lidocaine Cream

Active ingredient

Lidocaine HCl 4% w/w

Purpose

Topical anesthetic

Uses

temporarily relieves pain and itching due to:

- minor cuts
- sunburn
- minor scrapes
- minor burns
- insect bites
- minor skin irritations

Warnings

For external use only.

When Using this Product

- do not use in or near the eyes
- do not use in large quantities, particularly over raw surfaces or blistered areas

Stop Use and Ask a Doctor If

- allergic reaction occurs
- condition worsens or does not improve within 7 days
- symptoms clear up and return within a few days
- redness, irritation, swelling, pain or other symptoms begin or increase

Keep Out of Reach of Children

If swallowed, get medical help or contact a Poison Control Center right away.

Directions

adults and children 2 years and older: apply externally to the affected area up to 3 to 4 times a day

children under 2 years: ask a doctor

Other Information

- May be applied under occlusive dressing.
- Store at 20-25°C (68-77°F); excursions permitted to 15-30°C (59-86°F). See USP Controlled Room Temperature.

Inactive Ingredients

Aqua (Deionized Water), Arnica Montana Flower Extract, Boswellia Serrata Extract, Cetearyl Alcohol, Chondroitin Sulfate, Dimethyl Sulfone (MSM), Ethylhexylglycerin, Glucosamine Sulfate, Glycerin, Glyceryl Stearate, C13-14 Isoparaffin, Isostearyl Palmitate, Laureth-7, PEG-100 Stearate, Phenoxyethanol, Polyacrylamide, Propylene Glycol, Sodium Polyacrylate, Stearic Acid, Triethanolamine.

Package/Label Principal Display Panel

LIDOCAINE 4%
Topical Anesthetic Cream

120 grams

NDC: 50488-6262-1

Manufactured for: Alexso Inc.
2317 Cotner Avenue Los Angeles, CA 90064
Tel: 888.495.6078 Web: www.alexso.com

Label